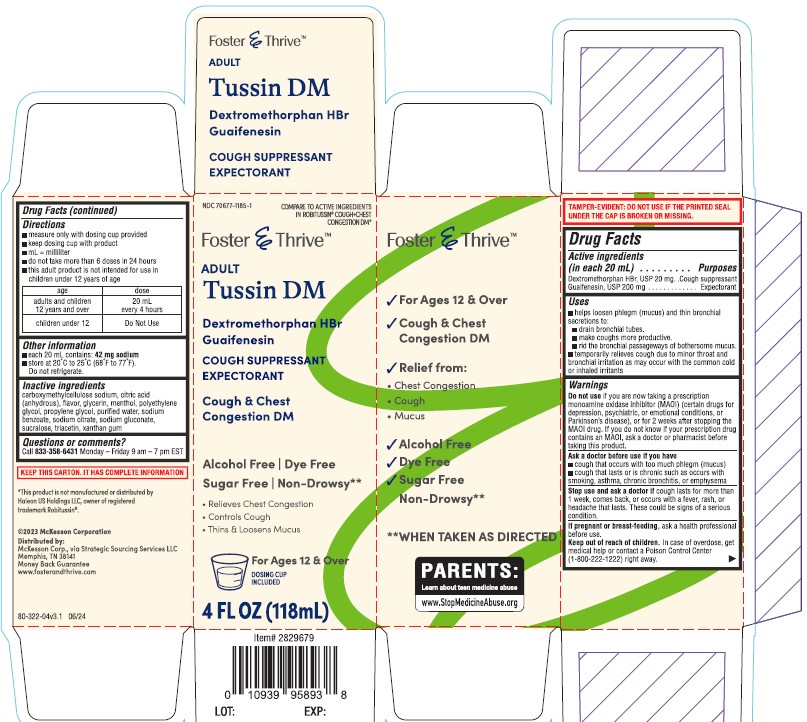 DRUG LABEL: Tussin DM
NDC: 70677-1185 | Form: SYRUP
Manufacturer: Strategic Sourcing Service, LLC
Category: otc | Type: HUMAN OTC DRUG LABEL
Date: 20241219

ACTIVE INGREDIENTS: GUAIFENESIN 200 mg/20 mL; DEXTROMETHORPHAN HYDROBROMIDE 20 mg/20 mL
INACTIVE INGREDIENTS: POLYETHYLENE GLYCOL 400; CARBOXYMETHYLCELLULOSE SODIUM; GLYCERIN; SUCRALOSE; MENTHOL; WATER; ANHYDROUS CITRIC ACID; PROPYLENE GLYCOL; SODIUM CITRATE, UNSPECIFIED FORM; SODIUM BENZOATE; TRIACETIN; SODIUM GLUCONATE; XANTHAN GUM

Foster and Thrive Cough and Chest Congestion DM Sugar Free Cough Syrup

Active ingredients (in each 20 mL)

Dextromethorphan HBr, USP 20 mg

Guaifenesin, USP 200 mg

Purposes

Cough suppressant

Expectorant

Uses

- helps loosen phlegm (mucus) and thin bronchial secretions to:
- drain bronchial tubes
- make coughs more productive
- rid bronchial passageways of bothersome mucus
- temporarily relieve cough due to minor throat and bronchial irritation as may occur with the common cold or inhaled irritants

Warnings

Do not use if you are now taking a prescription monoamine oxidase inhibitor (MAOI) (certain drugs for depression, psychiatric, or emotional conditions, or Parkinson's disease), or for 2 weeks after stopping the MAOI drug. If you do not know if your prescription drug contains an MAOI, ask a doctor or pharmacist before taking this product.

Ask a doctor before use if you have

- cough that occurs with too much phlegm (mucus)
- cough that lasts or is chronic such as occurs with smoking, asthma, chronic bronchitis, or emphysema

Stop use and ask a doctor if cough lasts for more than 1 week, comes back, or occurs with a fever, rash, or headache that lasts. These could be signs of a serious condition.

PREGNANCY OR BREAST FEEDING

If pregnant or breast-feeding, ask a health professional before use.

Keep out of reach of children.

In case of overdose, get medical help or contact a Poison Control Center right away.

Directions

- take every 4 hours
- do not take more than 6 doses in 24 hours

adults and children 12 years and over | 40 mL every 4 hours
children under 12 years | do not use

Other information

- store at 20º C to 25º C (68º F 77º F)
- do not refrigerate

Inactive ingredients

carboxymethylcellulose sodium, citric acid (anhydrous), flavor, glycerin, menthol, polyethylene glycol, propylene glycol, purified water, sodium benzoate, sodium citrate, sodium gluconate, sucralose, triacetin, xanthan gum

Questions or comments?

Call (833) 358-6431 Monday - Friday 9 am - 7 pm EST

PACKAGE LABEL

Foster & Thrive

Adult

Tussin DM

Dextromethorphan HBr

Guaifenesin

Cough Suppressant

Expectorant

Cough & Chest Congestion DM

Alcohol Free Dye Free Sugar Free

- Relieves chest congestion
- Controls cough
- Thins & loosens mucus

8 FL OZ (237 mL)